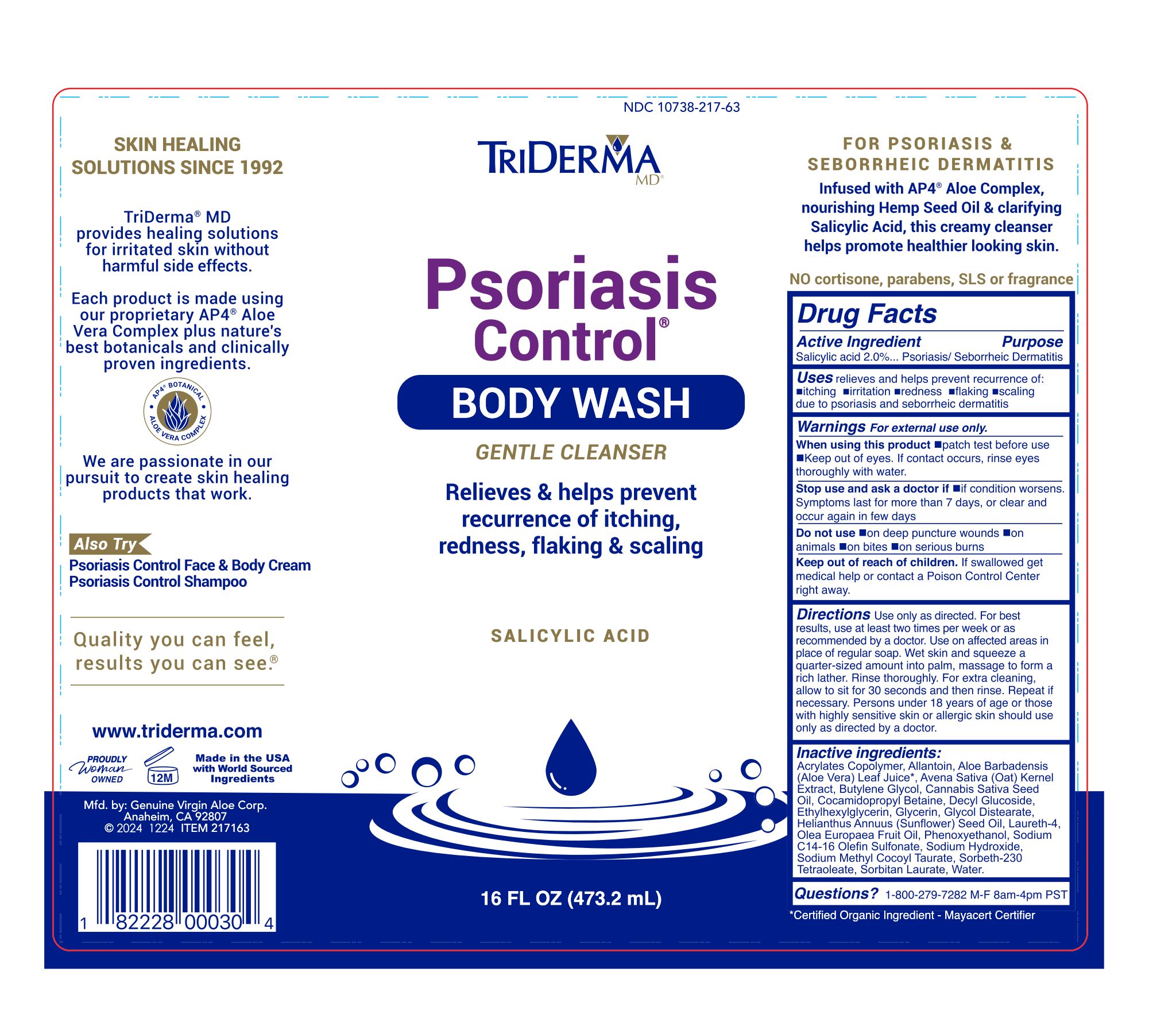 DRUG LABEL: TRIDERMA PSORIASIS CONTROL BODY WASH
NDC: 10738-217 | Form: GEL
Manufacturer: Genuine Virgin Aloe Corporation
Category: otc | Type: HUMAN OTC DRUG LABEL
Date: 20260124

ACTIVE INGREDIENTS: SALICYLIC ACID 2 g/100 mL
INACTIVE INGREDIENTS: AVENA SATIVA (OAT) KERNEL OIL; OLEA EUROPAEA (OLIVE) FRUIT OIL; GLYCOL DISTEARATE; SODIUM HYDROXIDE; LAURETH-4; SORBITAN LAURATE; ETHYLHEXYLGLYCERIN; SORBETH-30 TETRAOLEATE; HELIANTHUS ANNUUS (SUNFLOWER) SEED OIL; BUTYLENE GLYCOL; COCAMIDOPROPYL BETAINE; SODIUM METHYL COCOYL TAURATE; PHENOXYETHANOL; DECYL GLUCOSIDE; WATER; SODIUM C14-16 OLEFIN SULFONATE; ALOE VERA LEAF; CANNABIS SATIVA SEED OIL; GLYCERIN; ALLANTOIN

TRIDERMA PSORIASIS CONTROL BODY WASH

Active ingredient

Salicylic acid 2%

Purpose

Psoriasis/ Seborrheic Dermatitis

INDICATIONS AND USAGE

Uses relieves and helps prevent recurrence of:

•itching •irritation •redness •flaking •scaling due to psoriasis and seborrheic dermatitis

Warnings For external use only.

When using this product •patch test before use •Keep out of eyes. If contact occurs, rinse eyes thoroughly with water.

Stop use and ask a doctor if •if condition worsens. Symptoms last for more than 7 days, or clear and occur in few days

Do not use •on deep puncture wounds •on animals •on bites •on serious burns

Keep out of reach of children. If swallowed get medical help or contact a Poison Control Center right away.

DOSAGE AND ADMINISTRATION

Directions Use only as directed. For best results, use at least two times per week or as recommended by a doctor. Use on affected areas in place of regular soap or shampoo. Wet skin and / or scalp. Dispense a quarter-sized amount into palm, massage to form a rich lather. Rinse thoroughly. For extra cleaning, allow to sit for 30 seconds and then rinse. Repeat if necessary. Intended to be used by normally healthy adults only. Person under 18 years of age or those with highly sensitive skin or allergic skin should use only as directed by a doctor.

Inactive ingredients

Acrylates Copolymer, Allantoin, Aloe Barbadensis (Aloe Vera) Leaf Juice*, Avena Sativa (Oat) Kernel Extract, Butylene Glycol, Cannabis Sativa Seed Oil, Cocamidopropyl Betaine, Decyl Glucoside, Ethylhexylglycerin, Glycerin, Glycol Distearate, Helianthus Annuus (Sunflower) Seed Oil, Laureth-4, Olea Europaea Fruit Oil, Phenoxyethanol, Sodium C-14-16 Olefin Sulfonate, Sodium Hydroxide, Sodium Methyl Cocoyl Taurate, Sorbeth-230 Tetraoleate, Sorbitan Laurate, Water.

*Certified Organic Ingredient - Mayacert Certifier

Questions? 1-800-279-7282 www.triderma.com

GENTLE CLEANSER

Infused with AP4® Aloe* Complex, nourishing Hemp Seed Oil & clarifying Salicylic Acid, this creamy cleanser helps promote healthier looking skin.

No cortisone, parabens, added fragrance, SLS

EXPERTS IN SKIN HEALING SINCE 1992

TriDerma® MD provides healing solutions for irritated skin without harmful effects.

Each product is made using our proprietary AP4® Certified Organic Aloe* Complex plus nature's best botanicals and clinically proven ingredients.

We are passionate in our pursuit to create skin healing products that work.

Quality you can feel,

results you can see.®